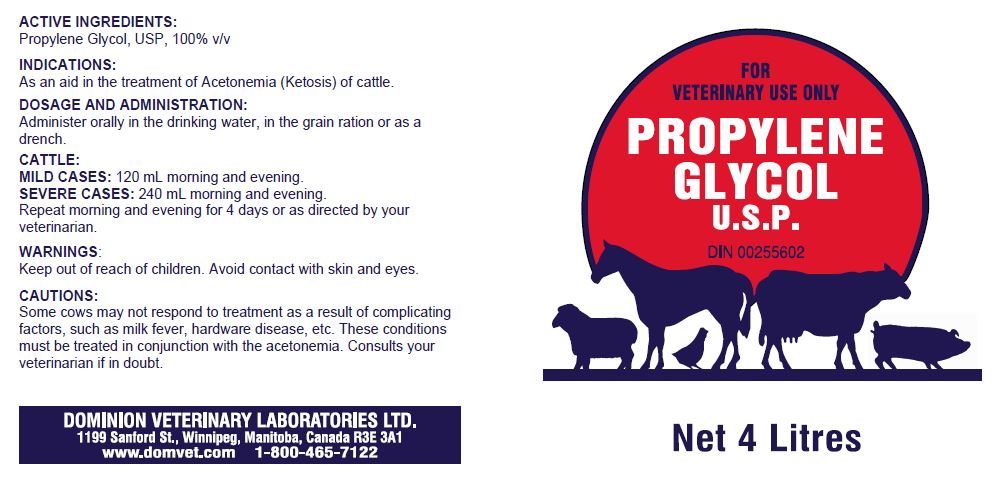 DRUG LABEL: PROPYLENE GLYCOL
NDC: 64120-107 | Form: LIQUID
Manufacturer: DOMINION VETERINARY LABORATORIES LTD.
Category: animal | Type: OTC ANIMAL DRUG LABEL
Date: 20211119

ACTIVE INGREDIENTS: PROPYLENE GLYCOL 100 g/100 mL

DOMINION VETERINARY LABORATORIES - PROPYLENE GLYCOL USP (64120-107)

INDICATIONS:

AS AN AID IN THE TREATMENT OF ACETONEMIA (KETOSIS) OF CATTLE.